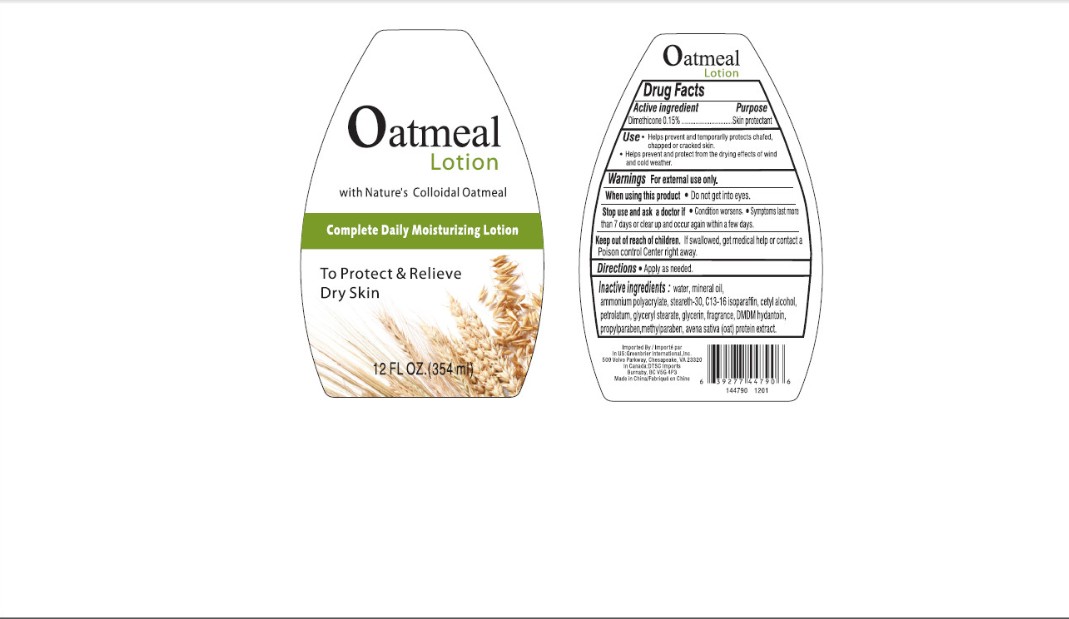 DRUG LABEL: Oatmeal
NDC: 33992-1129 | Form: LOTION
Manufacturer: GREENBRIER INTERNATIONAL
Category: otc | Type: HUMAN OTC DRUG LABEL
Date: 20111206

ACTIVE INGREDIENTS: dimethicone 0.15 g/100 g
INACTIVE INGREDIENTS: water; mineral oil; cetyl alcohol; petrolatum; glycerin; GLYCERYL MONOSTEARATE; dmdm hydantoin; propylparaben; methylparaben; steareth-30

Drug Facts

Active Ingredient Purpose

Dimethicone 0.15% Skin Protectant

PURPOSE

Help prevent and temporarily protects chafed, chapped or cracked skin.
Helps prevent and protect from the drying effects of wind and cold weather.

KEEP OUT OF REACH OF CHILDREN

If swallowed, get medical help or contact a Poison Control Center right away.

INDICATIONS AND USAGE

Apply as needed, and do not get into eyes.

Stop use and ask a doctor if Condition worsens; Symptoms last more than 7 days or clear up and occur again within a few days.

DOSAGE AND ADMINISTRATION

apply as needed

INACTIVE INGREDIENT

water, mineral oil, cetyl alcohol, glycerin, propylene glycol, methylparaben, propylparaben, DMDM hydantoin, steareth-30, ammonium polyacrylate, C13-16 isoparaffin, glyceryl stearate, fragrance, avena sativa (oat) protein extract